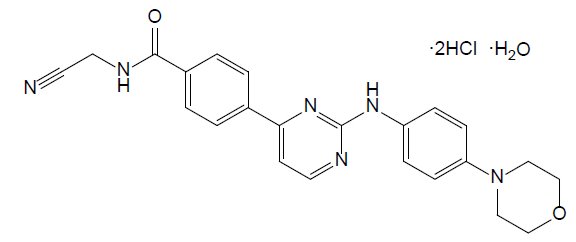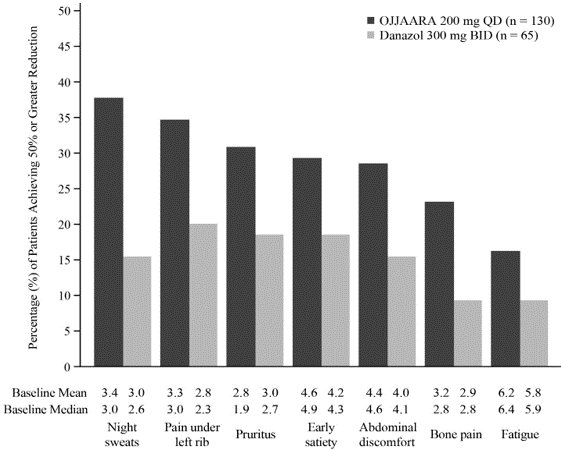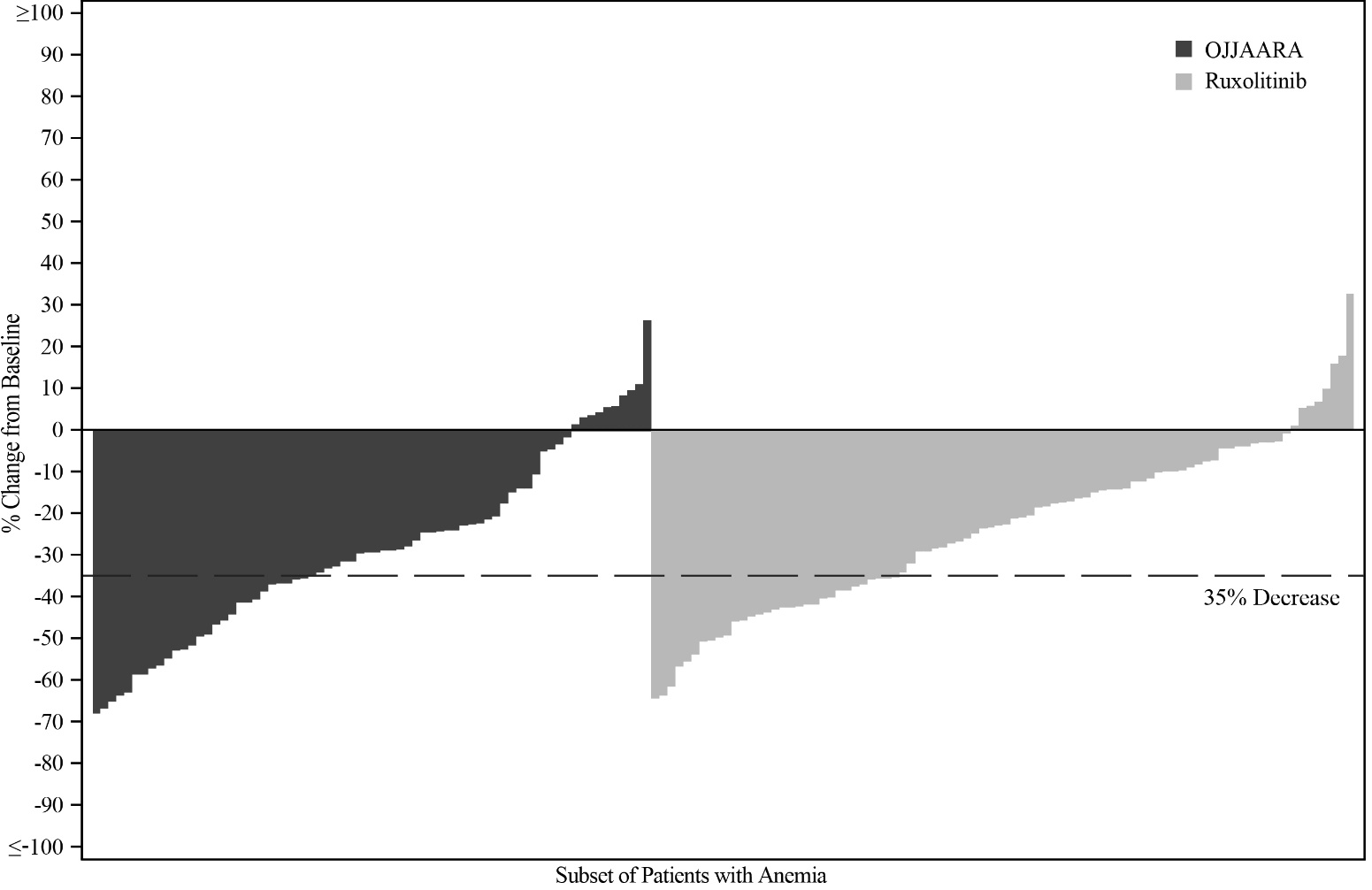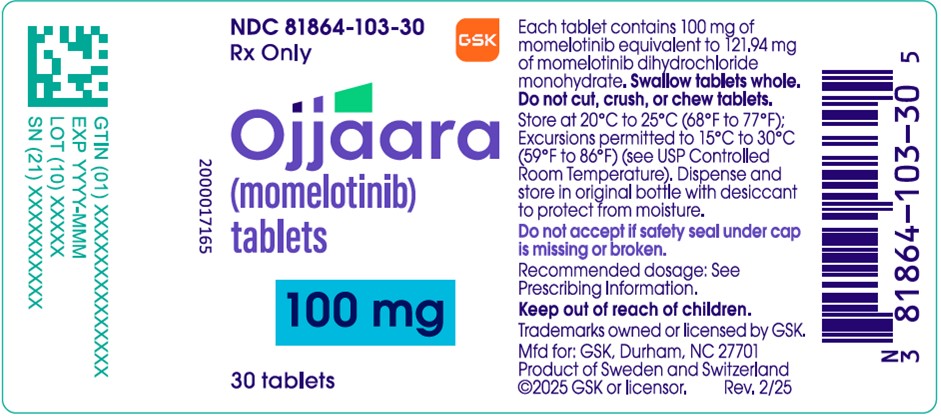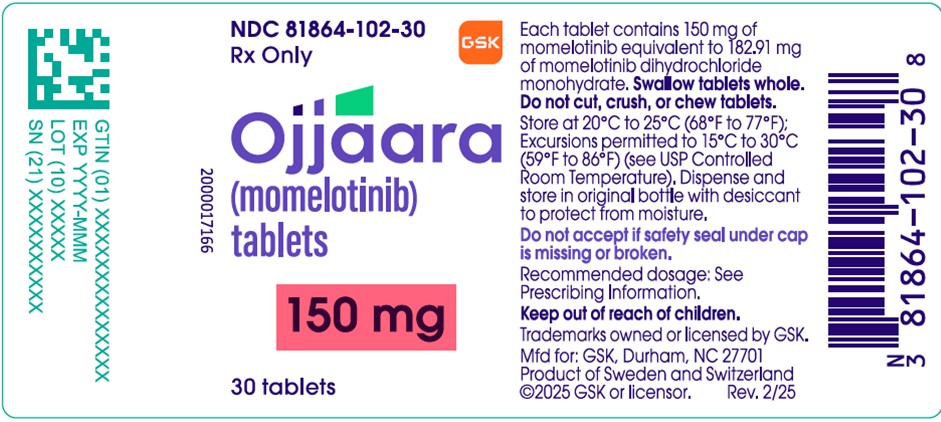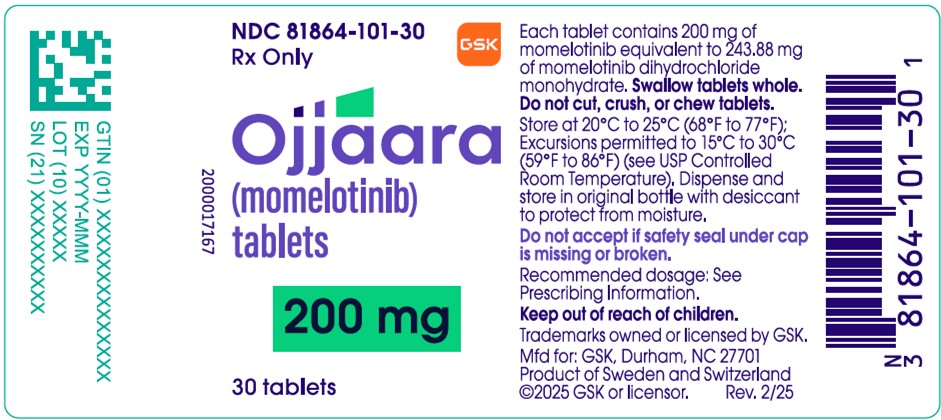 DRUG LABEL: Ojjaara
NDC: 81864-103 | Form: TABLET
Manufacturer: GlaxoSmithKline LLC
Category: prescription | Type: HUMAN PRESCRIPTION DRUG LABEL
Date: 20250418

ACTIVE INGREDIENTS: MOMELOTINIB DIHYDROCHLORIDE MONOHYDRATE 100 mg/1 1
INACTIVE INGREDIENTS: MICROCRYSTALLINE CELLULOSE; LACTOSE MONOHYDRATE; SODIUM STARCH GLYCOLATE TYPE A CORN; SILICON DIOXIDE; MAGNESIUM STEARATE; PROPYL GALLATE; POLYVINYL ALCOHOL, UNSPECIFIED; POLYETHYLENE GLYCOL, UNSPECIFIED; TALC; TITANIUM DIOXIDE; FERRIC OXIDE YELLOW; FERRIC OXIDE RED

HIGHLIGHTS OF PRESCRIBING INFORMATION

These highlights do not include all the information needed to use OJJAARA safely and effectively. See full prescribing information for OJJAARA.
OJJAARA (momelotinib) tablets, for oral use
Initial U.S. Approval: 2023

RECENT MAJOR CHANGES

Warnings and Precautions (5.4) | 4/2025

1 INDICATIONS AND USAGE

OJJAARA is a kinase inhibitor indicated for the treatment of intermediate or high-risk myelofibrosis (MF), including primary MF or secondary MF [post-polycythemia vera (PV) and post-essential thrombocythemia (ET)], in adults with anemia. (1)

2 DOSAGE AND ADMINISTRATION

- Recommended dosage: 200 mg orally once daily with or without food. (2.1)
- Severe hepatic impairment (Child-Pugh Class C): Reduce the starting dose to 150 mg orally once daily. (2.3)

3 DOSAGE FORMS AND STRENGTHS

Tablets: 100 mg, 150 mg, 200 mg. (3)

4 CONTRAINDICATIONS

None. (4)

5 WARNINGS AND PRECAUTIONS

- Risk of Infections: Do not initiate OJJAARA in patients with an active infection. Monitor for signs and symptoms of infection, including reactivation of hepatitis B, and initiate appropriate treatment promptly. (5.1)
- Thrombocytopenia and Neutropenia: Manage by dose reduction or interruption. (5.2)
- Hepatotoxicity: Obtain liver tests before initiation of and periodically throughout treatment with OJJAARA. (5.3)
- Severe Cutaneous Adverse Reactions (SCARs): Monitor for signs and symptoms, and interrupt OJJAARA until etiology of reaction has been determined. (5.4)
- Major Adverse Cardiovascular Events (MACE): Monitor for symptoms, evaluate and treat promptly. (5.5)
- Thrombosis: Evaluate and treat symptoms of thrombosis promptly. (5.6)
- Malignancies: Monitor for development of secondary malignancies, particularly in current or past smokers. (5.7)

6 ADVERSE REACTIONS

The most common adverse reactions (≥20% in either study) are thrombocytopenia, hemorrhage, bacterial infection, fatigue, dizziness, diarrhea, and nausea. (6.1)

To report SUSPECTED ADVERSE REACTIONS, contact GlaxoSmithKline at 1-888-825-5249 or FDA at 1-800-FDA-1088 or www.fda.gov/medwatch.

7 DRUG INTERACTIONS

- Organic Anion Transporting Polypeptide (OATP)1B1/B3 inhibitors: Monitor for adverse reactions. (7.1)
- Breast Cancer Resistance Protein (BCRP) substrates: Reduce rosuvastatin (BCRP substrate) dosage. Follow approved product information recommendations for other BCRP substrates. (7.2)

8 USE IN SPECIFIC POPULATIONS

- Pregnancy: May cause fetal harm. (8.1)
- Lactation: Advise not to breastfeed. (8.2)

FULL PRESCRIBING INFORMATION

1 INDICATIONS AND USAGE

OJJAARA is indicated for the treatment of intermediate or high-risk myelofibrosis (MF), including primary MF or secondary MF [post-polycythemia vera (PV) and post-essential thrombocythemia (ET)], in adults with anemia.

2 DOSAGE AND ADMINISTRATION

2.1 Recommended Dosage

The recommended dosage of OJJAARA is 200 mg orally once daily. OJJAARA may be taken with or without food.

Swallow OJJAARA tablets whole. Do not cut, crush, or chew tablets.

If a dose of OJJAARA is missed, the next scheduled dose should be taken the following day.

2.2 Laboratory Monitoring for Safety

Obtain the following blood tests prior to starting treatment with OJJAARA, periodically during treatment, and as clinically indicated:

- Complete blood count (CBC) with platelets [see Warnings and Precautions (5.2)]
- Hepatic panel [see Warnings and Precautions (5.3)]

2.3 Dosage Modification for Hepatic Impairment

The recommended starting dosage in patients with severe hepatic impairment (Child-Pugh Class C) is 150 mg orally once daily [see Use in Specific Populations (8.6)]. No dose adjustment is recommended for patients with mild or moderate hepatic impairment.

2.4 Dosage Modification for Adverse Reactions

Manage hematologic and non-hematologic adverse reactions as described in Table 1.

Table 1: Dose Modifications for OJJAARA-Related Adverse Reactions
Thrombocytopenia |  | Dose Modificationa
Baseline Platelet Count | Platelet Count | Dose Modificationa
≥100 × 10^9/L | 20 × 10^9/L to <50 × 10^9/L | Reduce daily dose by 50 mg from the last given dose.
≥100 × 10^9/L | <20 × 10^9/L | Interrupt treatment until platelets recover to 50 × 10^9/L.; Restart OJJAARA at a daily dose of 50 mg below the last given doseb.
≥50 × 10^9/L to <100 × 10^9/L | <20 × 10^9/L | Interrupt treatment until platelets recover to 50 × 10^9/L.; Restart OJJAARA at a daily dose of 50 mg below the last given doseb.
<50 × 10^9/L | <20 × 10^9/L | Interrupt treatment until platelets recover to baseline.; Restart OJJAARA at a daily dose of 50 mg below the last given doseb.
Neutropenia |  | Dose Modificationa
Absolute neutrophil count (ANC) <0.5 × 10^9/L |  | Interrupt treatment until ANC ≥0.75 × 10^9/L.; Restart OJJAARA at a daily dose of 50 mg below the last given doseb.
Hepatotoxicity; (unless other apparent causes) |  | Dose Modificationa
ALT and/or AST >5 × ULN (or >5 × baseline, if baseline is abnormal) and/or total bilirubin >2 × ULN (or >2 × baseline, if baseline is abnormal) |  | Interrupt treatment until AST and ALT ≤2 × ULN or baselinec and total bilirubin ≤1.5 × ULN or baselined.; Restart OJJAARA at a daily dose of 50 mg below the last given doseb.; If reoccurrence of ALT or AST elevations >5 × ULN, permanently discontinue OJJAARA.
Other Non-Hematologic |  | Dose Modificationa
Grade 3 or highere |  | Interrupt treatment until the toxicity resolves to Grade 1 or lower (or baseline).; Restart OJJAARA at a daily dose of 50 mg below the last given doseb.
ALT = alanine transaminase; AST = aspartate transaminase; ULN = upper limit of normal.
a Reinitiate or escalate treatment up to starting dosage as clinically appropriate.
b May reinitiate treatment at 100 mg if previously dosed at 100 mg.
c If baseline >2 × ULN.
d If baseline >1.5 × ULN.
e Graded using the National Cancer Institute Common Terminology Criteria for Adverse Events per (CTCAE).

Discontinue OJJAARA in patients unable to tolerate 100 mg once daily.

3 DOSAGE FORMS AND STRENGTHS

100 mg round tablet – brown with an underlined “M” debossed on one side and “100” on the other side.

150 mg triangular tablet – brown with an underlined “M” debossed on one side and “150” on the other side.

200 mg capsule-shaped tablet – brown with an underlined “M” debossed on one side and “200” on the other side.

4 CONTRAINDICATIONS

None.

5 WARNINGS AND PRECAUTIONS

5.1 Risk of Infections

Serious (including fatal) infections (e.g., bacterial and viral, including COVID-19) occurred in 13% of patients treated with OJJAARA. Infections regardless of grade occurred in 38% of patients treated with OJJAARA [see Adverse Reactions (6.1)]. Delay starting therapy with OJJAARA until active infections have resolved. Monitor patients receiving OJJAARA for signs and symptoms of infection and initiate appropriate treatment promptly.

Hepatitis B Reactivation

Hepatitis B viral load (HBV-DNA titer) increases, with or without associated elevations in alanine transaminase (ALT) or aspartate transaminase (AST), have been reported in patients with chronic hepatitis B virus (HBV) infection taking Janus Kinase (JAK) inhibitors, including OJJAARA. The effect of OJJAARA on viral replication in patients with chronic HBV infection is unknown. In patients with HBV infections, check hepatitis B serologies prior to starting OJJAARA. If HBsAg and/or anti-HBc antibody is positive, consider consultation with a hepatologist regarding monitoring for reactivation versus prophylactic hepatitis B therapy. Patients with chronic HBV infection who receive OJJAARA should have their chronic HBV infection treated and monitored according to clinical HBV guidelines.

5.2 Thrombocytopenia and Neutropenia

OJJAARA can cause thrombocytopenia and neutropenia [see Adverse Reactions (6.1)].

New or worsening thrombocytopenia, with platelet count less than 50 × 10^9/L, was observed in 20% of patients treated with OJJAARA. Eight percent of patients treated with OJJAARA had baseline platelet counts less than 50 × 10^9/L.

Severe neutropenia, absolute neutrophil count (ANC) less than 0.5 × 10^9/L, was observed in 2% of patients treated with OJJAARA.

Assess complete blood counts (CBC), including platelet and neutrophil counts, before initiating treatment and periodically during treatment as clinically indicated. Interrupt dosing or reduce the dose for thrombocytopenia or neutropenia [see Dosage and Administration (2.4)].

5.3 Hepatotoxicity

Two of the 993 patients with MF who received at least one dose of OJJAARA in clinical trials experienced reversible drug-induced liver injury. Overall, new or worsening elevations of ALT and AST (all grades) occurred in 23% and 24%, respectively, of patients treated with OJJAARA; Grade 3 and 4 transaminase elevations occurred in 1% and 0.5% of patients, respectively. New or worsening elevations of total bilirubin occurred in 16% of patients treated with OJJAARA. All total bilirubin elevations were Grades 1-2. The median time to onset of any grade transaminase elevation was 2 months, with 75% of cases occurring within 4 months.

Delay starting therapy in patients presenting with uncontrolled acute and chronic liver disease until apparent causes have been investigated and treated as clinically indicated. When initiating OJJAARA, refer to dosing in patients with hepatic impairment [see Dosage and Administration (2.3)].

Monitor liver tests at baseline, every month for 6 months during treatment, then periodically as clinically indicated. If increases in ALT, AST or bilirubin related to treatment are suspected, modify OJJAARA dosage based upon Table 1 [see Dosage and Administration (2.4)].

5.4 Severe Cutaneous Adverse Reactions (SCARs)

Severe cutaneous adverse reactions, including toxic epidermal necrolysis (TEN), have been observed in some patients treated with OJJAARA.

If signs or symptoms of severe cutaneous reactions occur, interrupt OJJAARA until the etiology of the reaction has been determined. Consider early consultation with a dermatologist for evaluation and management.

If etiology is considered to be associated with OJJAARA, permanently discontinue and do not reintroduce OJJAARA in patients who have experienced SCARs or other life-threatening cutaneous reactions during OJJAARA treatment.

5.5 Major Adverse Cardiovascular Events (MACE)

Another JAK inhibitor increased the risk of MACE, including cardiovascular death, myocardial infarction, and stroke [compared with those treated with tumor necrosis factor (TNF) blockers] in patients with rheumatoid arthritis, a condition for which OJJAARA is not indicated.

Consider the benefits and risks for the individual patient prior to initiating or continuing therapy with OJJAARA, particularly in patients who are current or past smokers and patients with other cardiovascular risk factors. Inform patients receiving OJJAARA of the symptoms of serious cardiovascular events and the steps to take if they occur.

5.6 Thrombosis

Another JAK inhibitor increased the risk of thrombosis, including deep venous thrombosis, pulmonary embolism, and arterial thrombosis (compared with those treated with TNF blockers) in patients with rheumatoid arthritis, a condition for which OJJAARA is not indicated.

Evaluate patients with symptoms of thrombosis and treat appropriately.

5.7 Malignancies

Another JAK inhibitor increased the risk of lymphoma and other malignancies excluding nonmelanoma skin cancer (NMSC) (compared with those treated with TNF blockers) in patients with rheumatoid arthritis, a condition for which OJJAARA is not indicated. Current or past smokers were at increased risk.

Consider the benefits and risks for the individual patient prior to initiating or continuing therapy with OJJAARA, particularly in patients with a known malignancy (other than a successfully treated NMSC), patients who develop a malignancy, and patients who are current or past smokers.

6 ADVERSE REACTIONS

The following clinically significant adverse reactions are described elsewhere in the labeling:

- Risk of Infections and Hepatitis B Reactivation [see Warnings and Precautions (5.1)]
- Thrombocytopenia and Neutropenia [see Warnings and Precautions (5.2)]
- Hepatotoxicity [see Warnings and Precautions (5.3)]
- Severe Cutaneous Adverse Reactions [see Warnings and Precautions (5.4)]
- Major Adverse Cardiovascular Events [see Warnings and Precautions (5.5)]
- Thrombosis [see Warnings and Precautions (5.6)]
- Malignancies [see Warnings and Precautions (5.7)]

6.1 Clinical Trials Experience

Because clinical trials are conducted under widely varying conditions, adverse reaction rates observed in the clinical trials of a drug cannot be directly compared with rates in the clinical trials of another drug and may not reflect the rates observed in practice.

The safety of OJJAARA was evaluated in 215 patients in 2 clinical trials (MOMENTUM and SIMPLIFY-1 anemic subgroup [hemoglobin (Hb) <10 g/dL]) [see Clinical Studies (14)].

MOMENTUM

Patients in the MOMENTUM trial had been previously treated with a JAK inhibitor and were randomly assigned 2:1 to receive double-blind OJJAARA 200 mg orally once daily (n = 130) or danazol 300 mg orally twice daily (n = 65) for 24 weeks, after which they were eligible to receive open-label OJJAARA in an extended treatment phase. Among patients who received OJJAARA, 72% were exposed for 24 weeks or longer and 52% were exposed for 48 weeks or longer [see Clinical Studies (14)].

Serious adverse reactions occurred in 35% of patients who received OJJAARA during the randomized treatment period of the MOMENTUM trial; the most common serious adverse reactions (≥2%) included bacterial infection (8%), viral infection (5%), hemorrhage (4%), acute kidney injury (3%), pneumonia (3%), pyrexia (3%), thrombosis (3%), syncope (2%), thrombocytopenia (2%), and renal and urinary tract infection (2%). Fatal adverse reactions occurred in 12% of patients who received OJJAARA; the most common (≥2%) fatal adverse reaction was viral infection (5%).

Permanent discontinuation of OJJAARA due to an adverse reaction occurred in 18% of patients during the randomized treatment period of the MOMENTUM trial. Adverse reactions that resulted in permanent discontinuation (≥2%) included viral infection (2%) and thrombocytopenia (2%). Dosage reduction or treatment interruption due to an adverse reaction occurred in 34% of patients. Adverse reactions requiring dosage reduction and/or treatment interruption (≥2%) included thrombocytopenia (13%), bacterial infection (2%), diarrhea (2%), and neutropenia (2%).

Among the 130 patients treated with OJJAARA during the randomized treatment period of MOMENTUM, the most common adverse reactions (≥20%) were thrombocytopenia, diarrhea, hemorrhage, and fatigue (Table 2).

Table 2: Adverse Reactions Occurring in ≥5% of Patients Receiving OJJAARA during Randomized Treatment in MOMENTUM
Adverse Reaction | OJJAARA; n = 130 |  | Danazola; n = 65
 | All Gradesb; % | Grade ≥3; % | All Grades; % | Grade ≥3; %
Thrombocytopeniac | 28 | 22 | 17 | 12
Diarrheac | 22 | 0 | 9 | 2
Hemorrhagec | 22 | 2 | 18 | 8
Fatiguec | 21 | 2 | 20 | 5
Nauseac | 16 | 2 | 9 | 3
Bacterial infectionc,d | 15 | 8 | 18 | 8
Abdominal painc | 13 | 1 | 18 | 3
Viral infectionc,d | 12 | 5 | 3 | 0
Pruritusc | 11 | 2 | 11 | 0
Elevated liver enzymesc | 10 | 2 | 9 | 3
Pyrexiac | 10 | 2 | 8 | 0
Coughc | 8 | 0 | 5 | 0
Paresthesiac | 8 | 1 | 2 | 0
Dizzinessc | 8 | 2 | 2 | 0
Vomitingc | 8 | 1 | 0 | 0
Rashc | 6 | 0 | 11 | 0
Renal and urinary tract infectionc,d | 6 | 2 | 11 | 5
Arrhythmiac | 5 | 1 | 6 | 2
Neutropenia | 5 | 5 | 3 | 3
a Study was not designed to evaluate meaningful comparisons of the incidence of adverse reactions across treatment groups.
b Adverse reactions graded using CTCAE v.5.
c Grouped term includes other related terms.
d Excludes opportunistic infections.

SIMPLIFY-1

Patients in the SIMPLIFY-1 trial were JAK inhibitor naïve and randomly assigned 1:1 to receive double-blind OJJAARA 200 mg orally once daily (n = 215) or ruxolitinib 5 to 20 mg orally twice daily (n = 217). Upon completion of the double-blind treatment phase, all patients were eligible to receive OJJAARA during the open-label phase. The safety of OJJAARA was evaluated in the population of patients with MF who were anemic at study entry. SIMPLIFY-1 enrolled 180 anemic patients who received OJJAARA (n = 85) or ruxolitinib (n = 95). Among these anemic patients who received OJJAARA, 78% were exposed for 24 weeks or longer and 61% were exposed for 48 weeks or longer [see Clinical Studies (14)].

Serious adverse reactions occurred in 28% of the anemic patients who received OJJAARA during the randomized treatment period of the SIMPLIFY-1 trial; the most common serious adverse reactions (≥2%) included bacterial infection (7%), pneumonia (6%), heart failure (4%) arrhythmia (2%), and respiratory failure (2%). A fatal adverse reaction (bacterial infection) occurred in 1 patient who received OJJAARA.

Permanent discontinuation of OJJAARA due to an adverse reaction occurred in 19% of the anemic patients during the randomized treatment period of the SIMPLIFY-1 trial. Adverse reactions that resulted in permanent discontinuation of OJJAARA (≥2%) included bacterial infection (2%), dizziness (2%), fatigue (2%), hypotension (2%), and thrombocytopenia (2%). Dosage reductions or treatment interruptions of OJJAARA due to an adverse reaction occurred in 21% of patients. Adverse reactions requiring dosage reduction and/or treatment interruption (≥2%) were thrombocytopenia (8%), pneumonia (4%), bacterial infection (2%), abdominal pain (2%), elevated liver enzymes (2%), and hypotension (2%).

Among the 85 anemic patients treated with OJJAARA during the randomized treatment period of SIMPLIFY-1, the most common adverse reactions (≥20%) were dizziness, fatigue, bacterial infection, hemorrhage, thrombocytopenia, diarrhea, and nausea (Table 3).

Table 3: Adverse Reactions Occurring in ≥5% of Anemic Patients Receiving OJJAARA during Randomized Treatment in SIMPLIFY-1
Adverse Reactions | OJJAARA; n = 85; Baseline Hb <10 g/dL |  | Ruxolitiniba; n = 95; Baseline Hb <10 g/dL
Adverse Reactions | All Gradesb; % | Grade ≥3; % | All Grades; % | Grade ≥3; %
Dizzinessc | 24 | 1 | 15 | 2
Fatiguec | 22 | 0 | 25 | 1
Bacterial infectionc,d | 21 | 8 | 12 | 2
Hemorrhagec | 21 | 1 | 18 | 2
Thrombocytopeniac | 21 | 11 | 34 | 6
Diarrheac | 20 | 1 | 20 | 1
Nauseac | 20 | 0 | 3 | 1
Abdominal painc | 18 | 1 | 14 | 1
Coughc | 14 | 0 | 11 | 0
Hypotensionc | 14 | 2 | 0 | 0
Pain in extremity | 12 | 0 | 5 | 0
Pyrexiac | 12 | 1 | 11 | 0
Rashc | 12 | 0 | 3 | 0
Renal and urinary tract infectionc,d | 12 | 1 | 4 | 0
Elevated liver enzymesc | 11 | 4 | 9 | 0
Headachec | 11 | 0 | 16 | 0
Peripheral edema | 11 | 0 | 8 | 0
Arrhythmiac | 8 | 2 | 2 | 1
Paresthesiac | 8 | 0 | 3 | 0
Pneumoniac | 8 | 8 | 5 | 3
Vomitingc | 8 | 0 | 5 | 0
Back pain | 7 | 1 | 2 | 0
Viral infectionc,d | 6 | 0 | 13 | 2
Vitamin B1 deficiency | 6 | 0 | 7 | 0
a Study was not designed to evaluate meaningful comparisons of the incidence of adverse reactions across treatment groups.
b Adverse reactions graded using CTCAE v.4.03.
c Grouped term includes other related terms.
d Excludes opportunistic infections.

Other Adverse Reactions

Clinically relevant adverse reactions occurring in <5% of anemic patients in the MOMENTUM and SIMPLIFY-1 studies include:

Eye Disorders: Blurred vision.

Infections and Infestations: Fungal infection (excludes opportunistic infections).

Musculoskeletal and Connective Tissue Disorders: Arthralgia.

Nervous System Disorders: Neuralgia, peripheral neuropathy, peripheral motor neuropathy, polyneuropathy, syncope.

Vascular Disorders: Flushing.

6.2 Postmarketing Experience

The following adverse reactions have been identified during postapproval use of OJJAARA. Because these reactions are reported voluntarily from a population of uncertain size, it is not always possible to reliably estimate their frequency or establish a causal relationship to drug exposure.

Skin and Subcutaneous Tissue Disorders: Toxic epidermal necrolysis (TEN).

7 DRUG INTERACTIONS

7.1 Effect of Other Drugs on OJJAARA

Organic Anion Transporting Polypeptide (OATP)1B1/B3 Inhibitors

Momelotinib is an OATP1B1/B3 substrate. Concomitant use with an OATP1B1/B3 inhibitor increases momelotinib maximal concentrations (Cmax) and area under the concentration-time curve (AUC) [see Clinical Pharmacology (12.3)], which may increase the risk of adverse reactions with OJJAARA. Monitor patients concomitantly receiving an OATP1B1/B3 inhibitor for adverse reactions and consider OJJAARA dose modifications [see Dosage and Administration (2.4)].

7.2 Effect of OJJAARA on Other Drugs

Breast Cancer Resistance Protein (BCRP) Substrates

Momelotinib is a BCRP inhibitor. OJJAARA may increase exposure of BCRP substrates, which may increase the risk of BCRP substrate adverse reactions [see Clinical Pharmacology (12.3)]. When administered concomitantly with OJJAARA, initiate rosuvastatin (BCRP substrate) at 5 mg and do not increase to more than 10 mg once daily. Dose adjustment of other BCRP substrates may also be needed. Follow approved product information recommendations for other BCRP substrates.

8 USE IN SPECIFIC POPULATIONS

8.1 Pregnancy

Risk Summary

Available data on the use of OJJAARA in pregnant women are insufficient to determine whether there is a drug-associated risk for major birth defects or miscarriage. Based on animal reproduction studies conducted in rats and rabbits, momelotinib may cause embryo-fetal toxicity at exposures lower than the expected exposure in patients receiving 200 mg once daily (see Data). OJJAARA should only be used during pregnancy if the expected benefits to the mother outweigh the potential risks to the fetus.

The background risk of major birth defects and miscarriage for the indicated population is unknown. All pregnancies have a background risk of birth defect, loss, or other adverse outcomes. In the U.S. general population, the estimated background risk of major birth defects and miscarriage in clinically recognized pregnancies is 2% to 4% and 15% to 20%, respectively.

Data

Animal Data: In an embryofetal development study, pregnant rats received momelotinib 2, 6 or 12 mg/kg/day orally, during the period of organogenesis (Gestation Day 6 to 17). Embryo-fetal toxicity (embryonic death, soft tissue anomalies, skeletal variations, and lower mean fetal body weights) was observed at 12 mg/kg (in the presence of maternal toxicity). Skeletal variations were observed (in the absence of maternal toxicity) at 6 mg/kg/day at exposures 3.5 times the exposure at the recommended human dose of 200 mg daily based on combined momelotinib and M21 (a major human metabolite) AUC. No developmental toxicity was observed at 2 mg/kg/day at exposures equivalent to the recommended dose (based on combined momelotinib and M21 AUC).

In an embryofetal developmental study, pregnant rabbits received momelotinib at 7.5, 30 or 60 mg/kg/day orally during the period of organogenesis (Gestation Day 7 to 20). Momelotinib was associated with maternal toxicity at 60 mg/kg/day, which resulted in reduced mean fetal weight, delayed bone ossification, and an abortion at less than the exposure at the recommended dose (based on combined momelotinib and M21 AUC). No developmental toxicity was observed at lower doses tested in rabbits.

In a pre- and post-natal development study, pregnant rats received momelotinib 2, 6 or 12 mg/kg/day orally from organogenesis through lactation (Gestation Day 6 to lactation Day 20). Decreased pup body weights and embryo-lethality were observed in the dams administered 6 and 12 mg/kg/day. Pup survival was significantly reduced in the 12 mg/kg/day group from birth to Day 4 of lactation. Momelotinib exposure in dams at 12 mg/kg and 6 mg/kg were approximately 2 times the exposure at the recommended dose (based on combined momelotinib and M21 AUC). The exposure in dams at the No Observed Adverse Effect Level (NOAEL) dose of 2 mg/kg was less than the exposure at the recommended dose (based on combined momelotinib and M21 AUC).

8.2 Lactation

Risk Summary

There are no data on the presence of momelotinib or its metabolites in human milk, the effects on the breastfed child, or the effects on milk production. It is not known whether OJJAARA is excreted in human milk. Momelotinib was present in rat pups following nursing from treated dams with adverse effects observed in the offspring. When a drug is present in animal milk, it is likely that the drug will be present in human milk. Because of the potential for serious adverse reactions in a breastfed child, patients should not breastfeed during treatment with OJJAARA, and for at least 1 week after the last dose of OJJAARA.

Data

Animal Data: In a pre- and postnatal development study, momelotinib was administered orally to rats during the lactation period; the drug was detected in plasma of nursing pups, which adversely affected pup survival.

8.3 Females and Males of Reproductive Potential

Contraception

Advise females of reproductive potential who are not pregnant to use highly effective contraception during therapy and for at least 1 week after the last dose of OJJAARA.

8.4 Pediatric Use

The safety and effectiveness of OJJAARA in pediatric patients have not been established.

8.5 Geriatric Use

There were 275 patients aged 65 years and older in the clinical studies for MF [see Clinical Studies (14)]. Of the total number of OJJAARA-treated patients in these studies, 163/216 (75%) were aged 65 years and older, and 63/216 (29%) were aged 75 years and older. No overall differences in safety or effectiveness of OJJAARA have been observed between patients aged 65 years and older and younger adult patients.

8.6 Hepatic Impairment

The recommended starting dose of OJJAARA in patients with severe hepatic impairment (Child-Pugh C) is 150 mg orally once daily [see Dosage and Administration (2.3)]. No dose modification is recommended for patients with mild hepatic impairment (Child-Pugh A) or moderate hepatic impairment (Child-Pugh B).

Momelotinib is extensively metabolized [see Clinical Pharmacology (12.3)]. Momelotinib exposure increased with severe hepatic impairment (Child-Pugh C). No clinically significant changes in momelotinib exposure were observed in subjects with mild hepatic impairment (Child-Pugh A) or moderate hepatic impairment (Child-Pugh B) [see Clinical Pharmacology (12.3)].

10 OVERDOSAGE

There is no known antidote for overdose with OJJAARA. If overdose is suspected, the patient should be monitored for signs or symptoms of adverse reactions or effects, and appropriate supportive treatment should be instituted immediately. Further management should be as clinically indicated. Hemodialysis is not expected to enhance the elimination of momelotinib.

Consider contacting the Poison Help line (1-800-222-1222) or a medical toxicologist for additional overdose management recommendations.

11 DESCRIPTION

OJJAARA contains momelotinib dihydrochloride monohydrate, which is a kinase inhibitor with the chemical name N‑(Cyanomethyl)-4-(2-{[4-(morpholin-4-yl)phenyl]amino}pyrimidin-4-yl)benzamide dihydrochloride monohydrate. It has a molecular formula of C23H22N6O2●2HCl●H2O, molecular weight of 505.40 and the following structural formula:

Momelotinib dihydrochloride monohydrate is a light yellow to brown to reddish-brown solid and is slightly soluble in water and insoluble in aqueous buffers across a pH range of 2.1 to 9. Momelotinib free base has a molecular formula of C23H22N6O2 and a molecular weight of 414.47.

OJJAARA (momelotinib) tablets are for oral administration. Each tablet contains 100 mg, 150 mg, or 200 mg of momelotinib, which is equivalent to 121.94 mg, 182.91 mg, or 243.88 mg, respectively, of momelotinib dihydrochloride monohydrate as the active ingredient. The core of each tablet contains the following inactive ingredients: lactose monohydrate, magnesium stearate, microcrystalline cellulose, propyl gallate, silicon dioxide, and sodium starch glycolate. The film coating of each tablet contains the following inactive ingredients: polyethylene glycol, polyvinyl alcohol, red iron oxide, talc, titanium dioxide, and yellow iron oxide.

12 CLINICAL PHARMACOLOGY

12.1 Mechanism of Action

Momelotinib is an inhibitor of wild type Janus Kinase 1 and 2 (JAK1/JAK2) and mutant JAK2V617F, which contribute to signaling of a number of cytokines and growth factors that are important for hematopoiesis and immune function. Momelotinib and its major human circulating metabolite, M21, have higher inhibitory activity for JAK2 compared to JAK3 and tyrosine kinase 2 (TYK2). Momelotinib and M21 additionally inhibit activin A receptor type 1 (ACVR1), also known as activin receptor like kinase 2 (ALK2), which produces subsequent inhibition of liver hepcidin expression and increased iron availability resulting in increased red blood cell production. MF is a myeloproliferative neoplasm associated with constitutive activation and dysregulated JAK signaling that contributes to inflammation and hyperactivation of ACVR1. JAK signaling recruits and activates STAT (signal transducers and activation of transcription) proteins resulting in nuclear localization and subsequent regulation of gene transcription.

12.2 Pharmacodynamics

Momelotinib inhibited STAT3 phosphorylation in whole blood from patients with MF. Maximal inhibition of STAT3 phosphorylation occurred 2 hours after momelotinib dosing and inhibition persisted for at least 6 hours [see Clinical Pharmacology (12.1)]. Iron availability and erythropoiesis was assessed by analysis of circulating hepcidin concentrations. An acute and sustained reduction of circulating hepcidin was observed for the duration of the 24-week administration of momelotinib to patients with MF [see Clinical Pharmacology (12.1)].

Cardiac Electrophysiology

Momelotinib did not prolong the QT interval to any clinically relevant extent at 4 times the highest recommended dosage of 200 mg.

12.3 Pharmacokinetics

Momelotinib pharmacokinetic parameters are presented as mean (%CV) and were derived in patients with MF unless otherwise specified.

The momelotinib steady-state Cmax is 479 ng/mL (61%) and AUC is 3,288 ng•h/mL (60%) at the maximum recommended dosage. Momelotinib exposure (i.e., Cmax and AUC) increases dose proportionally from 100 mg to 300 mg (0.5 to 1.5 times the maximum recommended dosage), but less than dose‑proportional at doses from 400 mg to 800 mg (2 to 4 times the maximum recommended dosage). There is no clinically significant accumulation.

Absorption

Median time to momelotinib Cmax (Tmax) at steady state is 2 hours (Q1: 1 hour; Q3: 3 hours) post dose.

Effect of Food

No clinically significant differences in momelotinib pharmacokinetics were observed following administration of either a high-fat meal (800 kcal; 50% fat) or low-fat meal (400 kcal; 20% fat) in healthy subjects.

Distribution

Momelotinib steady state apparent volume of distribution is 984 L (118%). Momelotinib plasma protein binding is approximately 91% in healthy volunteers.

Elimination

The elimination half-life of momelotinib and the M21 metabolite is 4 to 8 hours. Momelotinib clearance is 103 L/h (87%).

Metabolism: Momelotinib is metabolized by multiple cytochrome P450 (CYP) enzymes including CYP3A4 (36%), CYP2C8 (19%), CYP2C9 (17%), CYP2C19 (19%), and CYP1A2 (9%).

M21 is an active human metabolite that has approximately 40% of the pharmacological activity of the parent. M21 is formed by CYP followed by aldehyde oxidase metabolism of momelotinib. The mean M21 to momelotinib ratio for AUC ranged from 1.4 to 2.1.

Excretion: Following a single oral dose of radiolabeled momelotinib, 69% (13% unchanged) of radioactivity was excreted in feces and 28% (<1% unchanged) in urine. Approximately 12% of the administered dose was excreted in urine as M21.

Specific Populations

No clinically significant differences in momelotinib and M21 pharmacokinetics were observed based on age (range: 28 to 92 years), race (83% White, 6% Asian, 2% Black), sex (60% male), weight (range: 34 kg to 138 kg), renal impairment (eGFR: 16.4 mL/min/1.73 m^2 to above 120 mL/min/1.73 m^2), or mild or moderate hepatic impairment (Child-Pugh A or B). The effect of end stage renal disease receiving dialysis on momelotinib pharmacokinetics is unknown.

Patients with Hepatic Impairment: Momelotinib Cmax increased by 13% and AUC increased by 97% in subjects with severe hepatic impairment (Child-Pugh C). The M21 metabolite Cmax decreased by 76% and AUC decreased by 48% in subjects with severe hepatic impairment (Child-Pugh C).

Drug Interaction Studies

Clinical Studies

OATP1B1/1B3 Inhibitors: Momelotinib Cmax increased by 40% and AUC increased by 57% following concomitant use with a single dose of a OATP1B1/1B3 inhibitor (rifampin). The M21 metabolite Cmax increased by 6% and AUC increased by 12%.

BCRP Substrates: A BCRP substrate (rosuvastatin) Cmax increased by 220% and AUC increased by 170% following concomitant use of a single dose of rosuvastatin at 10 mg with multiple doses of momelotinib (200 mg once daily).

Other Drugs: No clinically significant differences in momelotinib and M21metabolite pharmacokinetics were observed when used concomitantly with a strong CYP3A4 inducer (tested with multiple-dose rifampin), a strong CYP3A4 inhibitor (ritonavir), or an acid reducing agent (omeprazole, a proton pump inhibitor).

No clinically significant differences in the pharmacokinetics of a CYP3A4 substrate (midazolam) were observed when used concomitantly with momelotinib.

In Vitro Studies

Cytochrome P450 (CYP) Enzymes: Momelotinib is a weak, reversible, time-independent inhibitor of CYP2B6 but does not inhibit CYP1A2, 2C8, 2C9, 2C19, 2D6, or 3A4/5. The M21 metabolite does not inhibit any of these CYP enzymes.

Momelotinib and M21 do not induce CYP3A4, CYP2C8, CYP2C9, or P-glycoprotein (P-gp).

Uridine diphosphate-glucuronosyltransferase (UGT): Momelotinib is an inhibitor of UGT1A1 and UGT1A9. The M21 metabolite is an inducer of UGT1A1.

Transporter Systems: Momelotinib and M21 are substrates in vitro for efflux transporters, P-gp and BCRP, and hepatic uptake transporters, OATP1B1/1B3. Momelotinib is an inhibitor of BCRP.

13 NONCLINICAL TOXICOLOGY

13.1 Carcinogenesis, Mutagenesis, Impairment of Fertility

The carcinogenicity potential of momelotinib was assessed in rasH2 transgenic mice and Sprague-Dawley rats. There was no evidence of tumorigenicity in male or female mice that received momelotinib doses up to 100 mg/kg/day for 26 weeks. In a 2-year oral carcinogenicity study in Sprague-Dawley rats, momelotinib caused benign Leydig cell tumors at a dose of 15 mg/kg/day (17 times the maximum recommended dose based on combined momelotinib and M21 AUC). The increase in Leydig cell adenomas was considered related to a rat-specific phenomenon (i.e., prolactin-dependent Leydig cell tumorigenesis).

Momelotinib was not mutagenic in a bacterial reverse mutation assay, or clastogenic in an in vitro chromosomal aberration assay with human peripheral blood lymphocytes or in vivo in a rat bone marrow micronucleus assay.

In fertility studies in rats, momelotinib was administered for at least 70 days (males) and 14 days (females) prior to cohabitation and up to the implantation day (gestation Day 7) at doses of 5, 25, and 68 mg/kg/day. Momelotinib reduced sperm concentration and motility and reduced testes and seminal vesicle weights at 25 mg/kg/day or greater (approximately 13 times the recommended dose based on combined momelotinib and M21 AUC) leading to reduced fertility at 68 mg/kg/day. In females, momelotinib reduced ovarian function (reproductive cycles and ovulation) at 68 mg/kg/day and decreased the number of pregnant females and increased pre- and post-implantation loss with most pregnant rats having total litter loss at 25 mg/kg/day or greater. Exposures at the NOAEL in male and female rats at 5 mg/kg/day are approximately 3-times the recommended dose (based on combined momelotinib and M21 AUC).

14 CLINICAL STUDIES

The efficacy of OJJAARA in the treatment of adults with intermediate 1, intermediate 2, or high-risk MF, including primary MF, post-PV MF or post-ET MF, as defined by the Dynamic International Prognostic Scoring System (DIPSS) or International Prognostic Scoring System (IPSS) for MF, was established in the MOMENTUM trial and in a subpopulation of adults with anemia in the SIMPLIFY-1 trial. All patients received a starting dosage of OJJAARA 200 mg once daily. Eligible patients had baseline platelet count of ≥25 × 10^9/L in MOMENTUM and ≥50 × 10^9/L in SIMPLIFY-1.

MOMENTUM

MOMENTUM (NCT04173494) was a double-blind, 2:1 randomized, active-controlled trial in 195 symptomatic and anemic adults with MF who had previously received an approved JAK inhibitor therapy. Patients were treated with OJJAARA 200 mg once daily or danazol 300 mg twice daily for 24 weeks, then switched to open-label treatment with OJJAARA.

The median age was 71 years (range 38 to 86 years) with 79% of patients aged 65 years and older, and 63% of patients were male. Overall, 81% of patients were White, 9% of patients were Asian, 2% of patients were Black, and 6% of patients were Hispanic or Latino. Sixty-four percent of patients had primary MF, 19% had post-PV MF, and 17% had post-ET MF. Five percent of patients had intermediate-1 risk, 57% had intermediate-2 risk, and 35% had high-risk disease. Within the 8 weeks prior to treatment, 79% of patients had received red blood cell (RBC) transfusions (median of 4 RBC units; interquartile range: 1-6). At baseline, 13% and 15% of patients were transfusion independent (defined as no red blood cell transfusions in the 12 weeks before the first dose and Hb ≥8 g/dL) in the OJJAARA and danazol groups, respectively. The baseline median Hb count was 8 g/dL and the median platelet count was 96 × 10^9/L (range 24 × 10^9/L to 733 × 10^9/L). The baseline median palpable spleen length was 11 cm below the left costal margin; the median central spleen volume measured by magnetic resonance imaging (MRI) or computed tomography (CT) was 2,105 cm^3 (range 609 cm^3 to 9,717 cm^3).

Symptoms were measured using the Myelofibrosis Symptom Assessment Form (MFSAF v4.0) diary. The MFSAF v4.0 patient diary, completed throughout the randomized treatment period, captured the core symptoms of MF: fatigue (weariness and tiredness), night sweats (or feeling hot or flushed), itching, abdominal discomfort (feeling pressure or bloating), pain under ribs on left side, feeling of fullness after beginning to eat, and bone pain. For each item, symptom scores, ranging from 0 (absent) to 10 (worst imaginable), were added to create a daily Total Symptom Score (maximum score of 70). At baseline, the mean MFSAF v4.0 Total Symptom Score was 28 in the OJJAARA group and 26 in the danazol group.

The efficacy of OJJAARA in the treatment of patients with primary or secondary MF and anemia was established based on a significantly higher percentage of patients treated with OJJAARA compared to danazol achieving a MFSAF v4.0 Total Symptom Score reduction of 50% or more at Week 24 compared with their own baseline score (Table 4). Other endpoints included transfusion independence, spleen volume response, MFSAF v4.0 Total Symptom Score change from baseline, and percentage of patients with no transfusions.

Table 4: Percent of Patients Achieving Symptom Reduction, Transfusion Independence, and Spleen Volume Reduction at Week 24 in MOMENTUM
 | OJJAARA n = 130 | Danazol n = 65 | P-value
Patients with MFSAF v4.0 Total Symptom Score Reduction of 50% or more, n (%) | 32 (25%) | 6 (9%) | <0.01
Treatment differencea; (95% CI) | 16%; (6, 26) |  | <0.01
Patients with Transfusion Independence (no transfusion or Hb <8 g/dL between Weeks 12 and 24), n (%) | 39 (30%) | 13 (20%) | 0.023
Non-inferiority treatment differencea, b; (95% CI) | 14%; (2, 25) |  | 0.023
Patients with Spleen Volume Reduction by 25% or More, n (%) | 51 (39%) | 4 (6%) | <0.0001
Treatment differencea; (95% CI) | 33%; (23, 44) |  | <0.0001
MFSAF v4.0 Total Symptom Score Change from Baselineb (SE) | -9.4 (1.1) | -3.1 (1.6) | 0.001
Treatment differencec; (95% CI) | -6.2; (-10, -2.4) |  | 0.001
Patients with Spleen Volume Reduction by 35% or More, n (%) | 29 (22%) | 2 (3%) | 0.001
Treatment differencea; (95% CI) | 18%; (10, 27) |  | 0.001
Patients with No Transfusionsc, d (during the 24-week treatment period), n (%) | 46 (35%) | 11 (17%) | 0.001
Treatment differencea; (95% CI) | 17%; (8, 26) |  | 0.001
a Analyses stratified by baseline MFSAF v4.0 Total Symptom Score (<22 vs. ≥22), baseline palpable spleen length below the left costal margin (<12 vs. ≥12 cm), and baseline red blood cell or whole blood units transfused in the 8-week period before randomization (0, 1-4, ≥5 units).
b Non-inferiority difference between OJJAARA response rate and 80% of danazol response rate.
c Least squares means and difference are reported.
d Eight subjects treated with OJJAARA and 3 subjects treated with danazol had no transfusion, but discontinued treatment prior to Week 24.

Figure 1 shows the percentage of patients treated with OJJAARA and danazol who achieved a 50% or greater reduction from baseline for each individual symptom in the MFSAF v4.0.

Figure 1: Percent of Patients Achieving a 50% or Greater Reduction in Individual MFSAF v4.0 Symptom Scores at Week 24a in MOMENTUM

BID = twice a day; QD = once daily.

a Thirty-six (27.7%) subjects treated with OJJAARA and 27 (41.5%) subjects treated with danazol discontinued treatment prior to Week 24.

SIMPLIFY-1

SIMPLIFY-1 (NCT01969838) was a double-blind, randomized, active-controlled trial in 432 adults with MF who had not previously received a JAK inhibitor. Patients were treated with OJJAARA 200 mg once daily or ruxolitinib adjusted dose twice daily for 24 weeks. Patients were eligible to switch to open-label OJJAARA after 24 weeks (without tapering of the JAK inhibitor received during the randomization period). The baseline characteristics and efficacy results provided are for the subset of patients who had anemia (Hb <10 g/dL) at baseline (n = 181).

The median age was 68 years (range 25 to 86 years) with 67% of patients aged 65 years and older, and 59% of patients were male. Eighty-one percent of patients were White, 8% of patients were Asian, 1% of patients were Black, and 2% of patients were Hispanic or Latino. Sixty-three percent of patients had primary MF, 13% had post-PV MF, and 24% had post-ET MF. Four percent of patients had intermediate-1 risk, 25% had intermediate-2 risk, and 71% had high-risk disease. At baseline, 29% and 44% of patients were transfusion independent in the groups treated with OJJAARA or ruxolitinib, respectively. The baseline median Hb measurement was 8.8 g/dL and the median platelet count was 193 × 10^9/L (range 54 × 10^9/L to 2,865 × 10^9/L). Median palpable spleen length at baseline was 12 cm below the left costal margin; the median spleen volume at baseline (measured by MRI or CT) was 1,843 cm^3 (range 352 cm^3 to 9,022 cm^3).

The efficacy of OJJAARA in the treatment of patients with MF in SIMPLIFY-1 was based on spleen volume response (reduction by 35% or greater). A numerically lower percent of patients treated with OJJAARA (25%) achieved a Total Symptom Score reduction of 50% or more at Week 24 compared with ruxolitinib (36%).

The spleen volume reduction results are presented in Table 5.

Table 5: Percent of Patientsa Achieving 35% or Greater Reduction from Baseline in Spleen Volume at Week 24 in SIMPLIFY-1
 | OJJAARA; n = 86 | Ruxolitinib; n = 95
Patients with Spleen Volume Reduction by 35% or More, n (%); (95% CI) | 27 (31.4%); (21.8, 42.3) | 31 (32.6%); (23.4, 43.0)
a Subset of patients with anemia (Hb <10 g/dL) at baseline.

Figure 2 shows the percent change from baseline in spleen volume for each patient at Week 24 in SIMPLIFY-1.

Figure 2: Percent Change from Baseline in Spleen Volume for Each Patient at Week 24 in SIMPLIFY-1a, b

a Subset of patients with anemia (Hb <10 g/dL) at baseline.
  b Missing data rates for OJJAARA and ruxolitinib were 19% and 8%.

16 HOW SUPPLIED/STORAGE AND HANDLING

OJJAARA (momelotinib) tablets are available as follows:

Table 6: OJJAARA Presentations
NDC Number | Strength | Description | Tablets per Bottle
NDC 81864-103-30 | 100 mg | Round-shaped brown film-coated tablet with “M” on one side and “100” on the other side. | 30
NDC 81864-102-30 | 150 mg | Triangular-shaped brown film-coated tablet with “M” on one side and “150” on the other side. | 30
NDC 81864-101-30 | 200 mg | Capsule-shaped brown film-coated tablet with “M” on one side and “200” on the other side. | 30

Store at 20°C to 25°C (68°F to 77°F); excursions permitted to 15°C to 30°C (59°F to 86°F) [see USP Controlled Room Temperature].

Dispense to patient in original bottle only. Store in original bottle to protect from moisture. Replace cap securely each time after opening. Do not discard desiccant.

17 PATIENT COUNSELING INFORMATION

Advise the patient to read the FDA approved patient labeling (Patient Information).

Infections

Inform patients that OJJAARA can increase the risk of infections (including COVID-19) and instruct them to promptly report to their healthcare provider any signs and symptoms of infection [see Warnings and Precautions (5.1)].

Thrombocytopenia and Neutropenia

Inform patients that OJJAARA can cause thrombocytopenia and neutropenia, and of the need to monitor complete blood count, including platelet and neutrophil counts, before and during treatment. Advise patients to observe for and report any bleeding to their healthcare provider [see Warnings and Precautions (5.2)].

Hepatotoxicity

Inform patients that OJJAARA can cause hepatotoxicity, and of the need to monitor liver blood tests before and during treatment [see Warnings and Precautions (5.3)].

Severe Cutaneous Adverse Reactions (SCARs)

Inform patients that SCARs have been reported in some patients treated with OJJAARA and instruct them to promptly report any signs and symptoms of SCARs to their healthcare provider [see Warnings and Precautions (5.4)].

Major Adverse Cardiovascular Events (MACE)

Advise patients that events of MACE including myocardial infarction, stroke, and cardiovascular death have been reported in clinical studies with another JAK inhibitor used to treat rheumatoid arthritis, a condition for which OJJAARA is not indicated. Advise patients, especially current or past smokers and patients with other cardiovascular risk factors, to be alert for the development of signs and symptoms of cardiovascular events and to report them to their healthcare provider [see Warnings and Precautions (5.5)].

Thrombosis

Advise patients that events of deep vein thrombosis (DVT) and pulmonary embolism (PE) have been reported in clinical studies with another JAK-inhibitor used to treat rheumatoid arthritis, a condition for which OJJAARA is not indicated. Advise patients to tell their healthcare provider if they develop any signs or symptoms of a DVT or PE [see Warnings and Precautions (5.6)].

Malignancies

Advise patients, especially current or past smokers, that lymphoma and other malignancies (excluding non-melanoma skin cancers (NMSC) have been reported in clinical studies with another JAK inhibitor used to treat rheumatoid arthritis, a condition for which OJJAARA is not indicated [see Warnings and Precautions (5.7)].

Pregnancy

- Advise pregnant women and females of reproductive potential of the potential risk to a fetus. Advise females to inform their prescriber of a known or suspected pregnancy [see Use in Specific Populations (8.1)].
- Advise females of reproductive potential who are not pregnant to use highly effective contraception during therapy and for 1 week after the last dose of OJJAARA [see Use in Specific Populations (8.3)].

Lactation

Advise patients not to breastfeed during treatment with OJJAARA and for at least 1 week after the last dose of OJJAARA [see Use in Specific Populations (8.2)].

Trademarks are owned by or licensed to the GSK group of companies.

GlaxoSmithKline
Durham, NC 27701

©2025 GSK group of companies or its licensor.

OJJ:2PI

PATIENT INFORMATION
OJJAARA (oh-JAR-uh)
(momelotinib)
tablets, for oral use

What is OJJAARA?

OJJAARA is a prescription medicine used to treat adults with certain types of myelofibrosis (MF) who have anemia. It is not known if OJJAARA is safe and effective in children.

Before taking OJJAARA, tell your healthcare provider about all of your medical conditions, including if you:

- have an infection. See “Risk of Infections” in the section “What are the possible side effects of OJJAARA?”.
- have or have had hepatitis B
- have or have had liver problems
- have had a heart attack, or have or have had other heart problems, or stroke
- have or have had a blood clot
- smoke or were a smoker in the past
- have or have had any other cancers
- are pregnant or plan to become pregnant. OJJAARA may harm your unborn baby.
Females who are able to become pregnant:
  1. You should use effective birth control (contraception) during treatment and for 1 week after the last dose of OJJAARA.
  2. Tell your healthcare provider right away if you think you are pregnant or become pregnant during treatment with OJJAARA.
- are breastfeeding or plan to breastfeed. It is not known if OJJAARA passes into your breast milk. You should not breastfeed during treatment and for 1 week after the last dose of OJJAARA. Talk to your healthcare provider about the best way to feed your baby during this time.

Tell your healthcare provider about all the medicines you take, including prescription and over-the-counter medicines, vitamins, and herbal supplements. Taking OJJAARA with certain other medicines may affect the amount of OJJAARA or the other medicines in your blood and may increase your risk of side effects.

Know the medicines you take. Keep a list of the medicines you take to show your healthcare provider and pharmacist when you get a new medicine.

How should I take OJJAARA?

- Take OJJAARA exactly as your healthcare provider tells you to take it.
- Take OJJAARA by mouth 1 time each day.
- Take OJJAARA with or without food.
- Swallow tablets whole. Do not cut, crush, or chew tablets.
- If you miss a dose of OJJAARA, skip the missed dose and take your next dose the following day at your regularly scheduled time. Do not take 2 doses at the same time to make up for the missed dose.
- Your healthcare provider will do blood tests before you start taking OJJAARA and during treatment.
- Do not change your dose or stop taking OJJAARA without first talking to your healthcare provider.
- Your healthcare provider may change your dose, temporarily stop, or permanently stop treatment with OJJAARA if you get certain side effects.
- If you take too much OJJAARA, call your healthcare provider or Poison Help line at 1-800-222-1222, or go to the nearest emergency room right away and take your bottle of OJJAARA with you.

What are the possible side effects of OJJAARA?

OJJAARA may cause serious side effects, including:

- Risk of Infections. People who take OJJAARA may develop serious infections that can lead to death, such as bacterial and viral infections, including COVID-19. If you have an active infection, your healthcare provider should not start treatment with OJJAARA until your infection is gone. If you have had hepatitis B for a long time (chronic), OJJAARA may cause your hepatitis B to become active again, and your healthcare provider will check your blood for active hepatitis B before starting treatment.
Your healthcare provider will monitor you and treat you for any infections that you get during treatment with OJJAARA.
Tell your healthcare provider right away if you develop any of the following symptoms of infection:

- fever
- chills
- cough
- breathing problems

- diarrhea
- vomiting
- pain or burning feeling when passing urine

- Low platelet and white blood cell counts. OJJAARA may cause new or worsening low platelet and white blood cell counts. Low platelet counts may increase your risk for bleeding and low white blood cell counts may increase your risk for infection. Your healthcare provider will do blood tests to check your blood counts before you start taking OJJAARA and during treatment. Tell your healthcare provider right away if you have any signs of bleeding during treatment with OJJAARA, including:

- unusual bleeding
- black or tarry stools

- bruising

- Liver problems. OJJAARA may cause new or worsening increased liver enzymes and bilirubin in your blood. Your healthcare provider will check your liver enzymes before starting treatment, every month for the first 6 months of treatment, and then as needed during treatment with OJJAARA. Your healthcare provider may stop treatment with OJJAARA if your liver enzymes increase. Tell your healthcare provider if you develop any of the following signs or symptoms of liver problems:

- tiredness
- loss of appetite
- pain in your right upper stomach area (abdomen)

- dark urine
- yellowing of your skin or the white part of your eyes

- Severe skin reactions. Severe skin reactions that can be life-threatening have occurred with OJJAARA. Tell your healthcare provider or get medical help right away if you get any of the following signs or symptoms of severe skin reactions, with or without fever:

- rash that keeps getting worse
- severe rash
- reddened skin
- flu-like symptoms

- skin pain or burning
- blistering of the lips, eyes, or mouth
- blisters on the skin
- skin peeling

- Major cardiovascular events such as heart attack, stroke, and death. Major cardiac events have happened, especially in people with cardiac risk factors and who are current or past smokers, while taking another Janus kinase (JAK) inhibitor to treat rheumatoid arthritis. OJJAARA is in the JAK family of medicines.
  Get emergency help right away if you have any symptoms of a heart attack or stroke while taking OJJAARA, including:
  - discomfort in your chest that lasts for more than a few minutes, or that goes away and comes back
  - severe tightness, pain, pressure, or heaviness in your chest, throat, neck, or jaw
  - pain or discomfort in your arms, back, neck, jaw, or stomach
  - shortness of breath with or without chest discomfort
  - breaking out in a cold sweat
  - nausea or vomiting
  - feeling lightheaded
  - weakness in one part or on one side of your body
  - slurred speech
- Blood clots. Blood clots in the veins of the legs (deep vein thrombosis [DVT]) and lungs (pulmonary embolism [PE]) have happened in some people taking another JAK inhibitor to treat rheumatoid arthritis, and may be life-threatening. Tell your healthcare provider if you have had blood clots in the veins of your legs or lungs in the past.
  Tell your healthcare provider right away if you have any signs and symptoms of blood clots during treatment with OJJAARA, including:
  - swelling, pain, or tenderness in one or both legs
  - sudden, unexplained chest pain
  - shortness of breath or difficulty breathing
- New cancers. New cancers, including lymphoma and other cancers, except non-melanoma skin cancer, have happened in some people taking another JAK inhibitor to treat rheumatoid arthritis. The risk of new cancers is further increased in people who smoke or who smoked in the past.

The most common side effects of OJJAARA include:

- low platelet count
- bleeding
- bacterial infection
- tiredness

- dizziness
- diarrhea
- nausea

These are not all of the possible side effects of OJJAARA.

Call your doctor for medical advice about side effects. You may report side effects to FDA at 1-800-FDA-1088.

How should I store OJJAARA?

- Store OJJAARA at room temperature between 68°F to 77°F (20°C to 25°C).
- Keep OJJAARA in its original bottle. The OJJAARA bottle contains a desiccant packet to help keep your tablets dry (protect from moisture). Keep the desiccant in the bottle.
- Tightly close the OJJAARA bottle after you take your dose.

Keep OJJAARA and all medicines out of the reach of children.

General information about the safe and effective use of OJJAARA.

Medicines are sometimes prescribed for purposes other than those listed in a Patient Information leaflet. Do not use OJJAARA for a condition for which it was not prescribed. Do not give OJJAARA to other people, even if they have the same symptoms that you have. It may harm them. You can ask your pharmacist or healthcare provider for information about OJJAARA that is written for health professionals.

What are the ingredients in OJJAARA?

Active ingredient: momelotinib dihydrochloride monohydrate

Inactive ingredients: lactose monohydrate, magnesium stearate, microcrystalline cellulose, propyl gallate, silicon dioxide, and sodium starch glycolate

Film coating: polyethylene glycol, polyvinyl alcohol, red iron oxide, talc, titanium dioxide, and yellow iron oxide

Trademarks are owned by or licensed to the GSK group of companies.

GlaxoSmithKline, Durham, NC 27701

For more information about OJJAARA, call 1-888-825-5249 or visit our website at www.OJJAARA.com.

©2025 GSK group of companies or its licensor.

OJJ:2PIL

This Patient Information has been approved by the U.S. Food and Drug Administration Revised: April 2025

PACKAGE LABEL

PRINICPAL DISPLAY PANEL

NDC 81864-103-30

Ojjaara

(momelotinib)

tablets

100 mg

Rx Only

GSK

30 Tablets

Each tablet contains 100 mg tablet of momelotinib equivalent to 121.94 mg of momelotinib dihydrochloride. Swallow tablets whole.

Do not cut, crush, or chew tablets.

Store at 20°C to 25°C (68°F to 77°F); Excursions permitted between 15°C to 30°C (59°F to 86°F). (see USP Controlled Room Temperature). Dispense and store in original bottle with desiccant to protect from moisture.

Do not accept if safety seal under cap is missing or broken.

Recommended dosage: See Prescribing Information

Keep out of reach of children.

Trademarks owned or licensed by GSK.

Mfd for: GSK Durham, NC 27701

Product of Sweden and Switzerland

©2025 GSK or licensor.

Rev. 5/25

2000017165

PACKAGE LABEL

PRINICPAL DISPLAY PANEL

NDC 81864-102-30

Ojjaara

(momelotinib)

tablets

150 mg

Rx Only

GSK

30 Tablets

Each tablet contains 150 mg of momelotinib equivalent to 182.91 mg of momelotinib dihydrochloride. Swallow tablets whole.

Do not cut, crush, or chew tablets.

Store at 20°C to 25°C (68°F to 77°F); Excursions permitted between 15°C to 30°C (59°F to 86°F). (see USP Controlled Room Temperature). Dispense and store in original bottle with desiccant to protect from moisture.

Do not accept if safety seal under cap is missing or broken.

Recommended dosage: See Prescribing Information

Keep out of reach of children.

Trademarks owned or licensed by GSK.

Mfd for: GSK Durham, NC 27701

Product of Sweden and Switzerland

©2025 GSK or licensor.

Rev. 2/25

2000017166

PACKAGE LABEL

PRINICPAL DISPLAY PANEL

NDC 81864-101-30

Ojjaara

(momelotinib)

Tablets

200 mg

Rx Only

GSK

30 Tablets

Each tablet contains 200 mg of momelotinib is equivalent to 243.88 mg of momelotinib dihydrochloride. Swallow tablets whole.

Do not cut, crush, or chew tablets.

Store at 20°C to 25°C (68°F to 77°F); Excursions permitted between 15°C to 30°C (59°F to 86°F). (see USP Controlled Room Temperature). Dispense and store in original bottle with desiccant to protect from moisture.

Do not accept if safety seal under cap is missing or broken.

Recommended dosage: See Prescribing Information

Keep out of reach of children.

Trademarks owned or licensed by GSK.

Mfd for: GSK Durham, NC 27701

Product of Sweden and Switzerland

©2025 GSK or licensor.

Rev. 2/25

2000017167